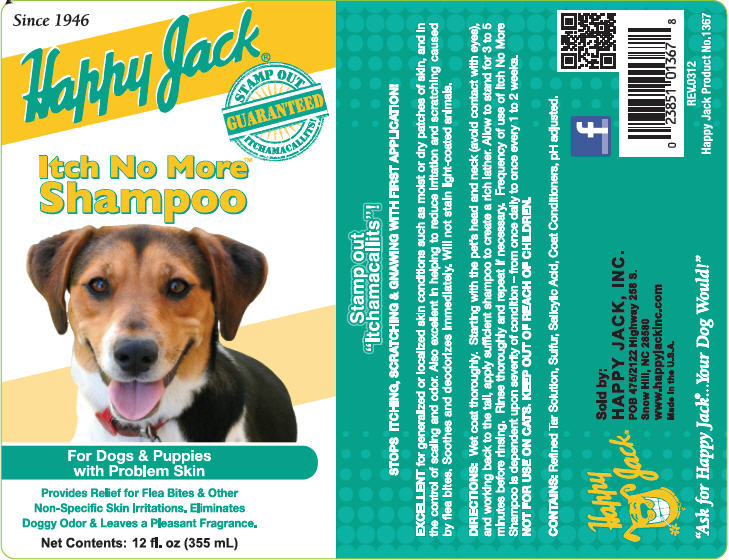 DRUG LABEL: Itch No More
NDC: 23851-367 | Form: SHAMPOO
Manufacturer: Happy Jack Inc
Category: animal | Type: OTC ANIMAL DRUG LABEL
Date: 20240119

ACTIVE INGREDIENTS: salicylic acid 20 mg/1 mL
INACTIVE INGREDIENTS: pine tar; sulfur; coal tar

Happy Jack®
Itch No More™
Shampoo

Stamp Out
"Itchamacallits"!
STOPS ITCHING, SCRATCHING & KNAWING WITH FIRST APPLICATION

VETERINARY INDICATIONS

EXCELLENT for generalized or localized skin conditions such as moist or dry patches of skin, and in the control of scaling and odor. Also excellent to reduce irritation and scratching caused by flea bites. Soothes and deodorizes immediately. Will not stain light-coated animals.

DIRECTIONS

Wet coat thoroughly. Starting with pet's head and neck (avoid contact with eyes), and working back to the tail, apply sufficient shampoo to create a rich lather. Allow to stand for 3 to 5 minutes before rinsing. Rinse thoroughly and repeat if necessary. Frequency of use of itch No More Shampoo is dependent upon severity of condition – from once daily to once every 1 to 2 weeks.

SAFE HANDLING WARNING

NOT FOR USE ON CATS. KEEP OUT OF REACH OF CHILDREN

CONTAINS

Refined Tar Solution, Sulfur, Salicylic Acid, Coat Conditioners, pH adjusted.

Sold by:

HAPPY JACK, INC.
POB 475/2122 Highway 258S.
Snow Hill, NC 28580
www.happyjackinc.com
Made in the U.S.A.

"Ask for Happy Jack®…Your Dog Would!"

Barcode
0 23851 01367 8
REV.0312
Happy Jack Products No.1367

PRINCIPAL DISPLAY PANEL - 355 mL Bottle Label

Since 1946

Happy Jack

Stamp Out
Guaranteed
Itchamacallits!

Itch No More
Shampoo

For Dogs & Puppies
with Problem Skin

Provides Relief for Flea Bites & Other
Non-Specific Skin Irritations. Eliminates
Doggy Odor & Leaves a Pleasant Fragrance.

Net Contents: 12 fl. oz (355 mL)